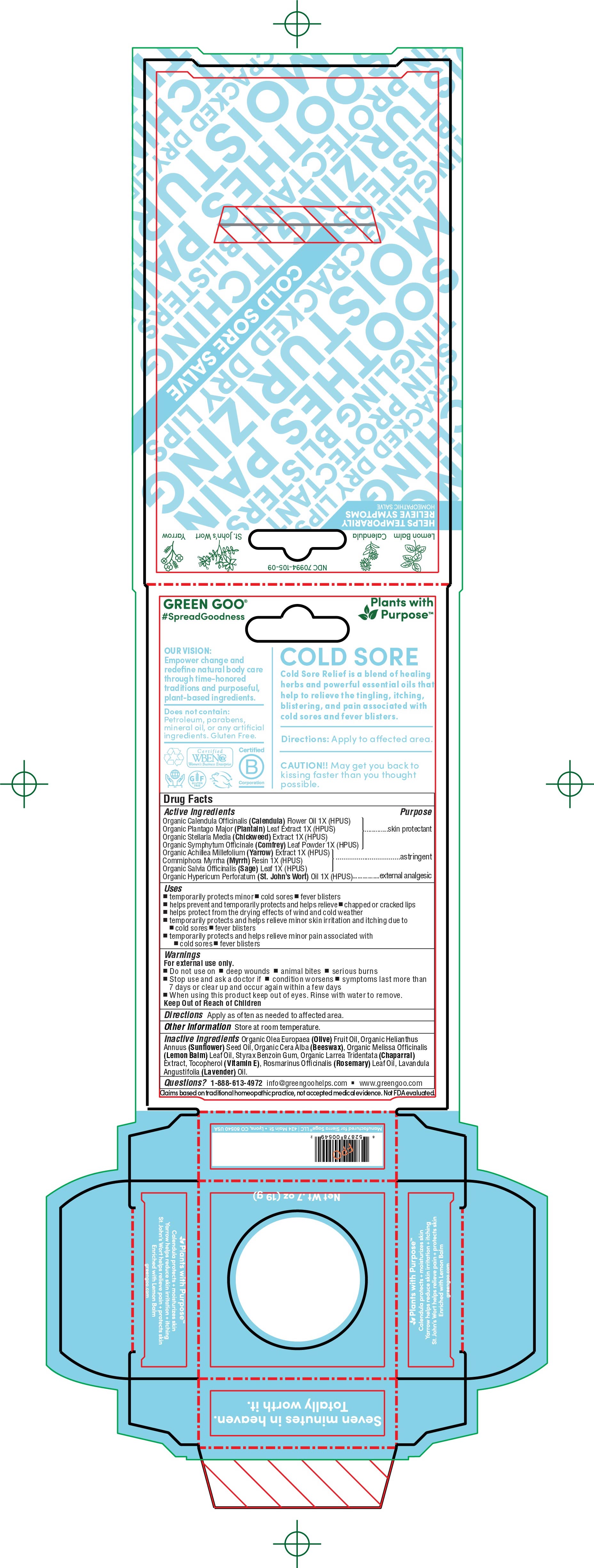 DRUG LABEL: Cold Sore Relief
NDC: 70994-105 | Form: SALVE
Manufacturer: Spry Life LLC
Category: homeopathic | Type: HUMAN OTC DRUG LABEL
Date: 20251215

ACTIVE INGREDIENTS: COMMIPHORA MYRRHA WHOLE 1 [hp_X]/19.8 g; COMFREY LEAF 1 [hp_X]/19.8 g; ACHILLEA MILLEFOLIUM FLOWER 1 [hp_X]/19.8 g; ST. JOHN'S WORT 1 [hp_X]/19.8 g; STELLARIA MEDIA 1 [hp_X]/19.8 g; SALVIA OFFICINALIS WHOLE 1 [hp_X]/19.8 g; CALENDULA OFFICINALIS FLOWER 1 [hp_X]/19.8 g; PLANTAGO MAJOR 1 [hp_X]/19.8 g
INACTIVE INGREDIENTS: YELLOW WAX; LARREA TRIDENTATA LEAF; ROSEMARY OIL; MELISSA OFFICINALIS; ALPHA-TOCOPHEROL; STYRAX BENZOIN RESIN; LAVENDER OIL; OLIVE OIL

Cold Sore Relief

Purpose Section

Skin Protectant

Astringent

External Analgesic

OTC Active Ingredients

Organic Calendula Officinalis (Calendula) Flower Oil 1X (HPUS)
Organic Plantago Major (Plantain) Leaf Extract 1X (HPUS)

Organic Stellaria Media (Chickweed) Extract 1X (HPUS)
Organic Symphytum Officinale (Comfrey) Leaf Powder 1X (HPUS)

Organic Achillea Millefofolium (Yarrow) Extract 1X (HPUS)
Commiphora Myrrha (Myrrh) Resin 1X (HPUS)
Organic Salvia Officinalis (Sage) Leaf 1X (HPUS)
Organic Hypericum Perforatum (St. Johns Wort) Oil 1X (HPUS)

Indications & Uses

• temporarily protects minor • cold sores • fever blisters

• temporarily protects and helps relieve • chapped or cracked lips
• helps protect from the drying effects of wind and cold weather

• temporarily protects and helps relieve minor skin irritation and itching due to • cold sores • fever blisters

• temporarily protects and helps relieves minor pain associated with • cold sores • fever blisters

Keep out of reach of children section

Keep out of reach of children.

Warnings Section

Warnings

For external use only.
-Do not use on • deep wounds • animal bites • serious burns

-Stop use and ask a doctor if • condition worsens • symptoms last more than 7 days or clear up and occur again within a few days
-When using this product keep out of eyes. Rinse with water to remove.

Storage and Handling

Store at room temperature.

Dosage & Administration Section

Apply as often as needed to affected area.

Inactive Ingredients

Organic Olea Europaea (Olive) Fruit Oil, Organic Helianthus Annuus (Sunflower) Seed Oil, Organic Cera Alba (Beeswax), Organic Melissa Officinale (Lemon Balm) Leaf Oil, Styrax Benzoin (Gum Benzoin) Gum, Organic Larrea Tridentata (Chapparal) Extract, Tocopherol (Vitamin E), Rosemarinus Officinalis (Rosemary) Leaf Oil, Lavandula Angustifolia (Lavender) Oil.